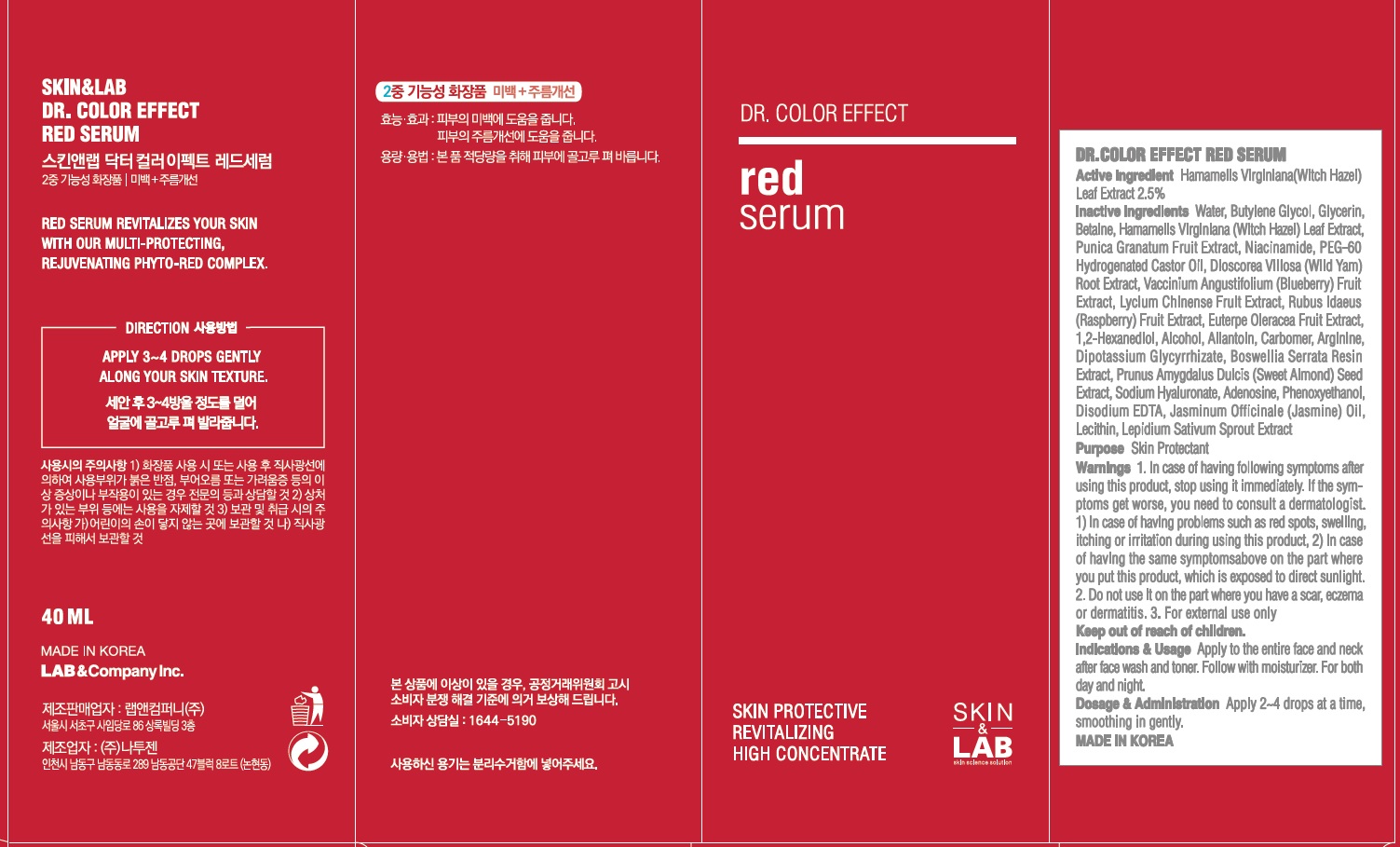 DRUG LABEL: DR COLOR EFFECT RED SERUM
NDC: 69457-010 | Form: CREAM
Manufacturer: LAB & Company Inc.
Category: otc | Type: HUMAN OTC DRUG LABEL
Date: 20180515

ACTIVE INGREDIENTS: Witch Hazel 1 g/40 mL
INACTIVE INGREDIENTS: Water; Butylene Glycol

ACTIVE INGREDIENT

Active Ingredient: Hamamelis Virginiana (Witch Hazel) Leaf Extract 2.5%

INACTIVE INGREDIENT

Inactive Ingredients:

Water, Butylene Glycol, Glycerin, Betaine, Punica Granatum Fruit Extract, Niacinamide, PEG-60 Hydrogenated Castor Oil, Dioscorea Villosa (Wild Yam) Root Extract, Vaccinium Angustifolium (Blueberry) Fruit Extract, Lycium Chinense Fruit Extract, Rubus Idaeus (Raspberry) Fruit Extract, Euterpe Oleracea Fruit Extract, 1,2-Hexanediol, Alcohol, Allantoin, Carbomer, Arginine, Dipotassium Glycyrrhizate, Boswellia Serrata Resin Extract, Prunus Amygdalus Dulcis (Sweet Almond) Seed Extract, Sodium Hyaluronate, Adenosine, Phenoxyethanol, Disodium EDTA, Jasminum Officinale (Jasmine) Oil, Lecithin, Lepidium Sativum Sprout Extract

PURPOSE

Purpose: Skin Protectant

WARNINGS

Warnings: 1. In case of having following symptoms after using this product, stop using it immediately. If the symptoms get worse, you need to consult a dermatologist. 1) In case of having problems such as red spots, swelling, itching or irritation during using this product, 2) In case of having the same symptoms above on the part where you put this product, which is exposed to direct sunlight. 2. Do not use it on the part where you have a scar, eczema or dermatitis. 3. For external use only

KEEP OUT OF REACH OF CHILDREN

INDICATIONS & USAGE

Indication and Usage: Apply to the entire face and neck after face wash and toner. Follow with moisturizer. For both day and night.

DOSAGE & ADMINISTRATION

Dosage and Administration: Apply 2-4 drops at a time, smoothing in gently.